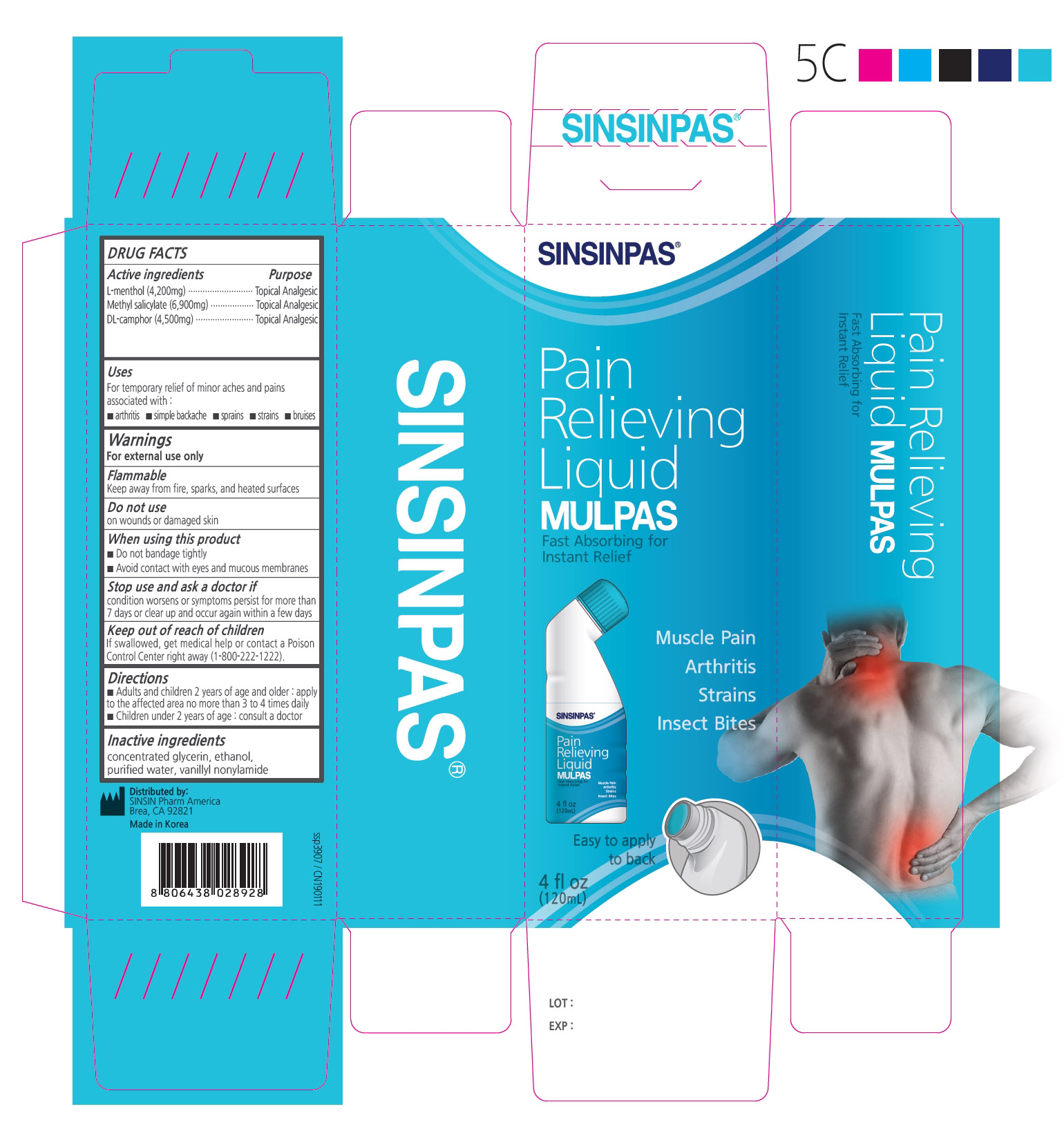 DRUG LABEL: SINSIN MULPAS
NDC: 55264-023 | Form: LIQUID
Manufacturer: Sinsin Pharmaceutical Co., Ltd.
Category: otc | Type: HUMAN OTC DRUG LABEL
Date: 20260220

ACTIVE INGREDIENTS: CAMPHOR (SYNTHETIC) 4500 mg/120 mL; METHYL SALICYLATE 6900 mg/120 mL; MENTHOL 4200 mg/120 mL
INACTIVE INGREDIENTS: NONIVAMIDE; GLYCERIN

SINSINPAS MULPAS PAIN RELIEVING LIQUID

ACTIVE INGREDIENT

L-menthol
Methyl salicylate
dl-camphor

PURPOSE

Topical Analgesic

Keep out of reach of children. If swallowed, get medical help or contact a Poison Control Center (1-800-222-1222) right away.

INDICATIONS AND USAGE

For the temporarily relief of minor aches and pains of muscles and joints associated with:

- Arthritis
- Simple backache
- Strains
- Bruises
- Sprains

WARNINGS

For external use only

Do not use

- on wounds or damaged skin
- if you are allergic to any ingredients of this product
- with a heating pad
- with, or at the same time as, other external analgesic products

When using this product

- do not use otherwise than directed
- avoid contact with eyes, mucous membranes or rashes
- do not bandage tightly

Ask a doctor before use if you are prone to allergic reaction from aspirin or salicylates

Stop use and ask a doctor if

- rash, itching, or excessive skin irritation develops
- conditions worsen
- symptoms persist for more than 7 days
- symptoms clear up and occur again within a few days

If pregnant or breast-feeding, ask a health professional before use.

Directions

Adults and children 2 years of age and over:

- Apply to affected area no more than 3 to 4 times daily
- Children undress 12 years of age: consult a doctor

INACTIVE INGREDIENT

concentrated glycerin, ethanol, purified water, vanillyl nonylamide.